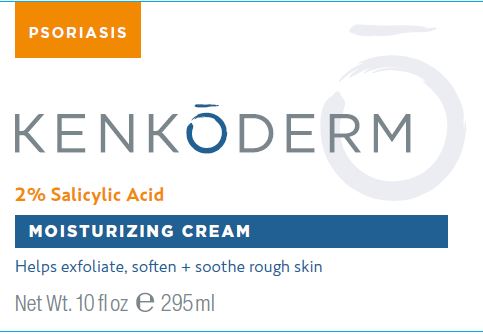 DRUG LABEL: Kenkoderm Psoriasis Moisturizing
NDC: 73632-004 | Form: CREAM
Manufacturer: Olympus Trading Company, LLC
Category: otc | Type: HUMAN OTC DRUG LABEL
Date: 20260109

ACTIVE INGREDIENTS: SALICYLIC ACID 2 g/100 g
INACTIVE INGREDIENTS: BEHENTRIMONIUM METHOSULFATE; HYALURONATE SODIUM; NIACINAMIDE; CERAMIDE NP; CERAMIDE 1; TOCOPHEROL; PHYTOSPHINGOSINE; CHOLESTEROL; SODIUM LAUROYL LACTYLATE; DIMETHICONE; CARBOMER HOMOPOLYMER, UNSPECIFIED TYPE; XANTHAN GUM; PHENOXYETHANOL; EDETATE DISODIUM ANHYDROUS; ETHYLHEXYLGLYCERIN; SODIUM HYDROXIDE; WATER; UREA; PROPYLENE GLYCOL; GLYCERYL STEARATE SE; CETOSTEARYL ALCOHOL; SHEA BUTTER; MEADOWFOAM SEED OIL; GLYCERIN; CETYL ALCOHOL; GLYCERYL MONOSTEARATE; PEG-100 STEARATE

Kenkoderm Psoriasis Moisturizing Cream

Active Ingredient

Salicylic Acid 2.0%

Purpose

Psoriasis

Uses

- For the relief of skin itching, scaling, redness, flaking and inflammation associated with psoriasis.
- Helps prevent the recurrence of the symptoms of psoriasis.

Warnings

For external use only

Ask a doctor before use if you have:

- a condition that covers a large area of the body
- an allergy or sensitivity to Salicylic Acid

Stop use and ask a doctor if

condition worsens or does not improve after regular use of this product as directed.

When using this product

avoid contact with the eyes. If contact occurs, rinse eyes thoroughly with water.

Keep out of reach of children.

If swallowed, get medical help or contact a Poison Control Center right away.

Directions

- Apply to affected areas one to four times daily or as directed by a doctor.

Other information

- Keep cap tightly closed when not in use.
- Store in a cool, dry location.

Inactive ingredients

Water (Aqua), Urea, Propylene Glycol, Glyceryl Stearate SE, Cetearyl Alcohol, Butyrospermum Parkii (Shea) Butter, Limnanthes Alba (Meadowfoam) Seed Oil, Glycerin, Cetyl Alcohol, Glyceryl Stearate, PEG-100 Stearate, Behentrimonium Methosulfate, Sodium Hyaluronate, Niacinamide, Ceramide NP, Ceramide AP, Ceramide EOP, Tocopherol, Phytosphingosine, Cholesterol, Sodium Lauroyl Lactylate, Dimethicone, Carbomer, Xanthan Gum, Phenoxyethanol, Disodium EDTA, Ethylhexylglycerin, Sodium Hydroxide

Questions or comments?

Call 1-703-829-7627

Principal Display Panel

Psoriasis

KENKODERM

2% Salicylic Acid
MOISTURIZING CREAM
Helps exfoliate, soften + soothe rough skin
Net Wt. 10 fl oz ℮295 ml

©2020 All rights reserved
Kenkoderm, Arlington, VA 22201
kenkoderm.com

NDC 73632-004-01 LOT#XXXXXXX

Label